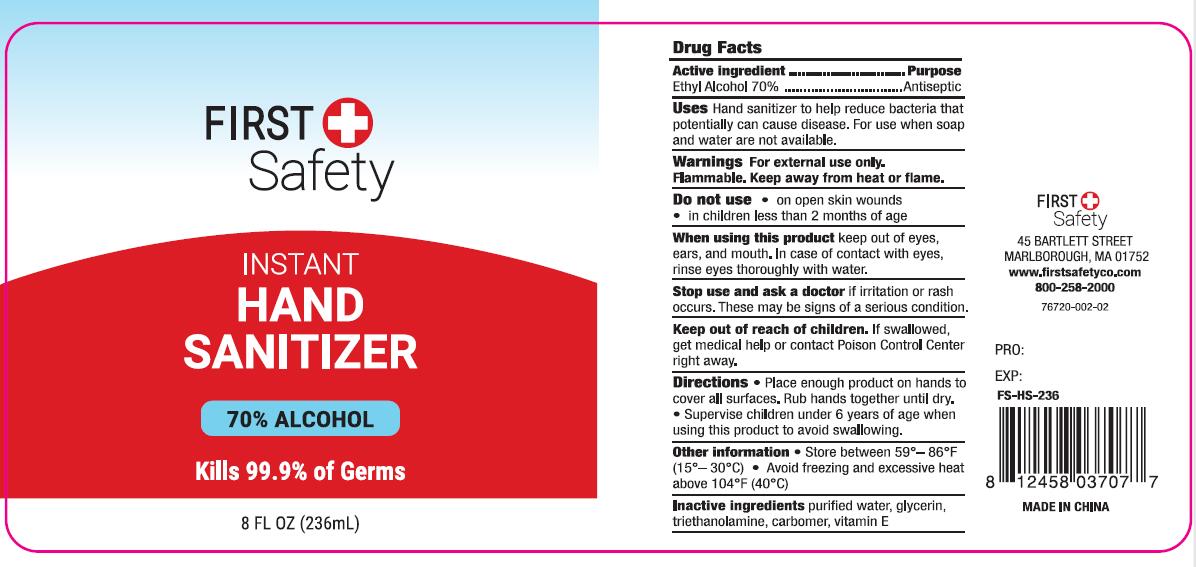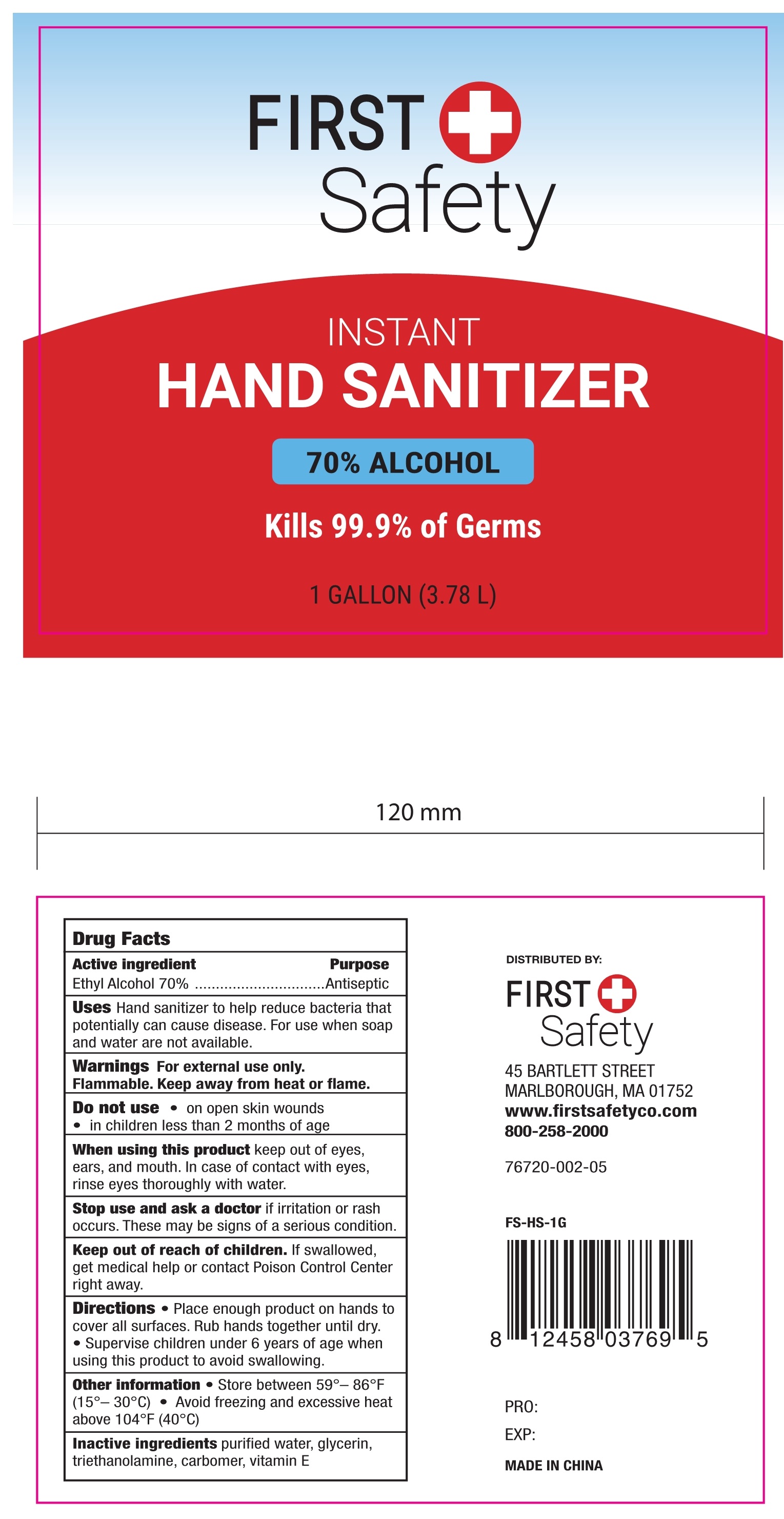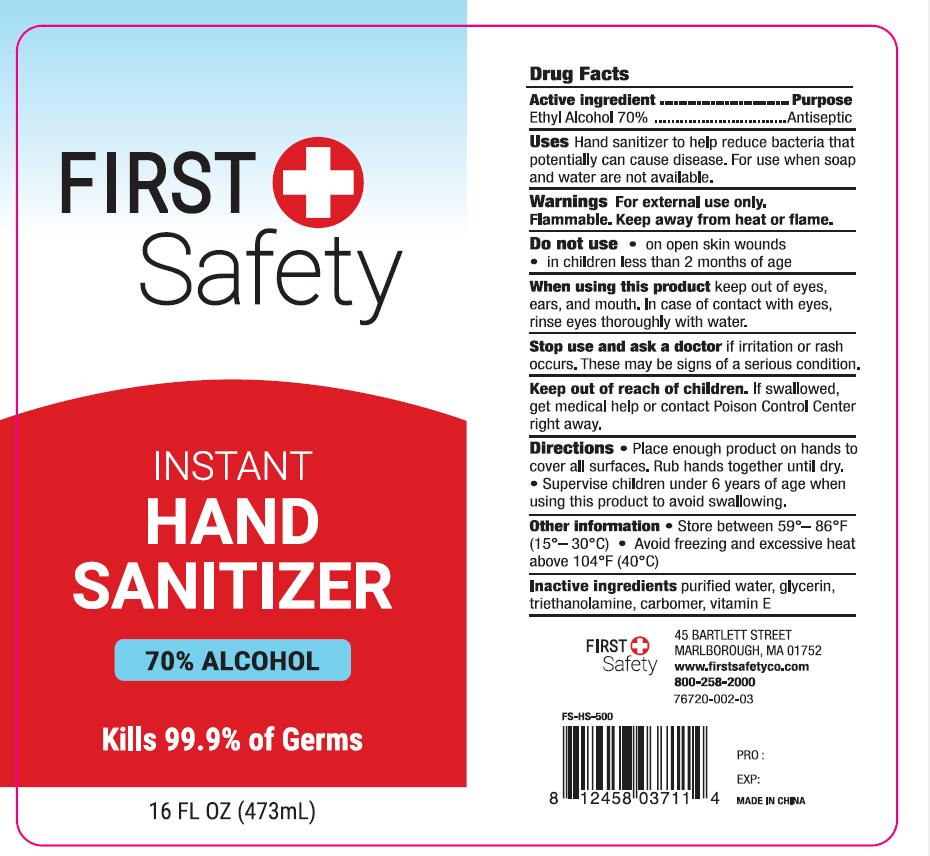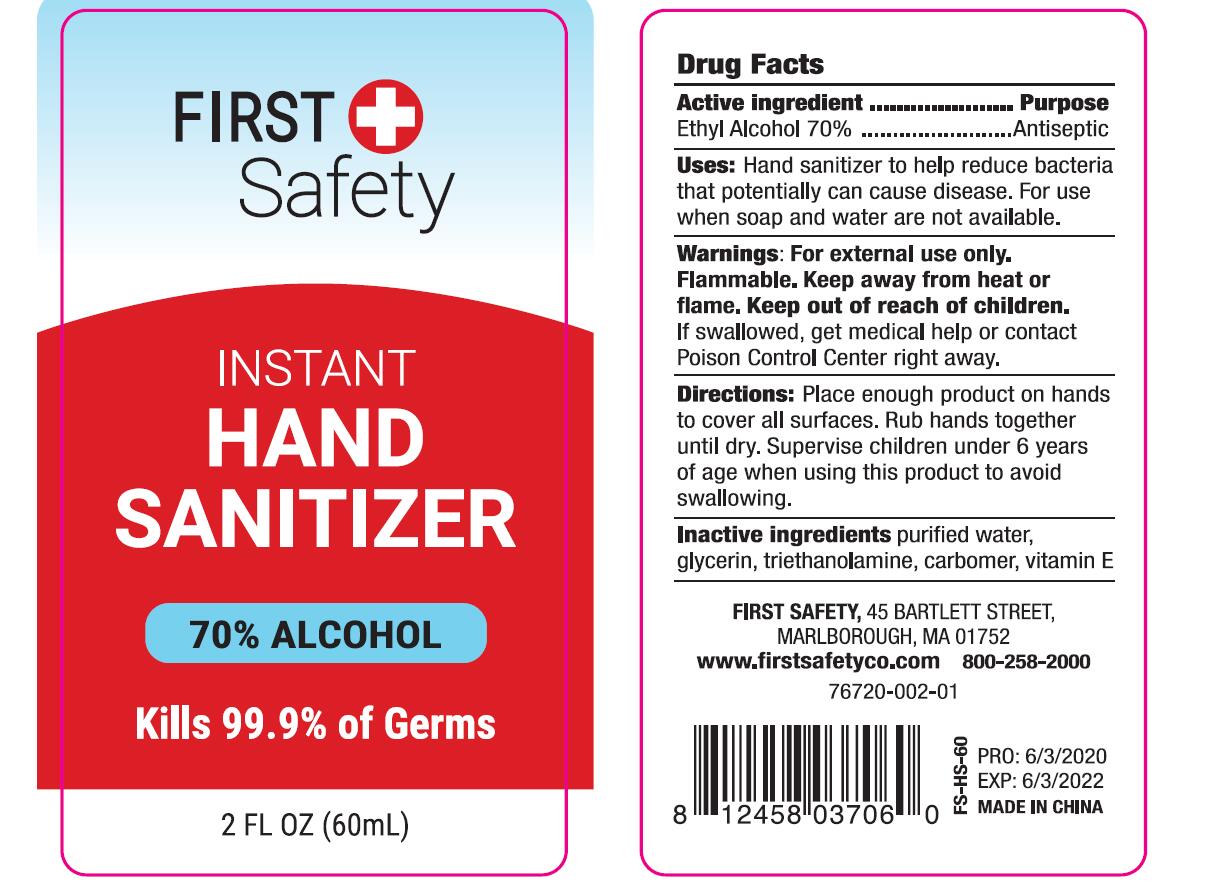 DRUG LABEL: HAND SANITIZER
NDC: 74763-002 | Form: GEL
Manufacturer: ZHEJIANG GAFLE AUTO CHEMICAL CO.,LTD
Category: otc | Type: HUMAN OTC DRUG LABEL
Date: 20220328

ACTIVE INGREDIENTS: ALCOHOL 70 mL/100 mL
INACTIVE INGREDIENTS: TROLAMINE; WATER; CARBOMER HOMOPOLYMER, UNSPECIFIED TYPE; GLYCERIN; .ALPHA.-TOCOPHEROL

HAND SANITIZER

ACTIVE INGERDIENT

Ethyl Alcohol 70%.

PURPOSE

Antiseptic

USES

Hand sanitizer to help reduce bacteria that potentially can cause disease. For use when soap and water are not available.

WARNINGS

For external use only.
Flammable. Keep away from heat or flame. Keep out of reach of children.
If swallowed, get medical help or contact
Poison Control Center right away.

KEEP OUT OF REACH OF CHILDREN

If swallowed, get medical help or contact
Poison Control Center right away.

DIRECTIONS

Place enough product on hands to cover all surfaces.

Rub hands together until dry. Supervise children under 6 years of age when using this product to avoid swalloWing.

OTHER INFORMATION

Store below 106°F.(41°C)

INACTIVE INGERDIENTS

Purified Water,Glycerin,Triethanolamine,Carbomer,Vitamin E.